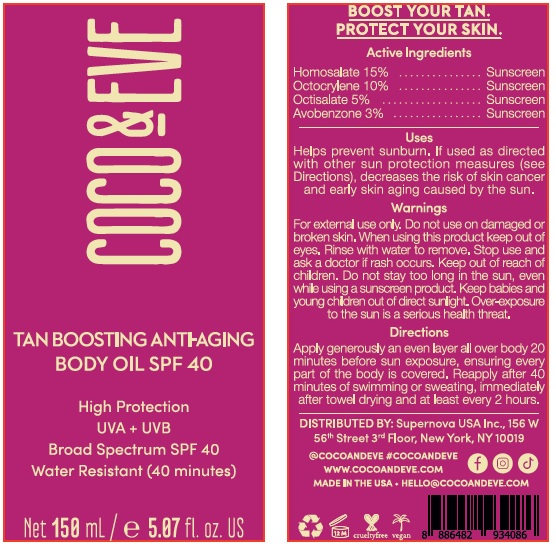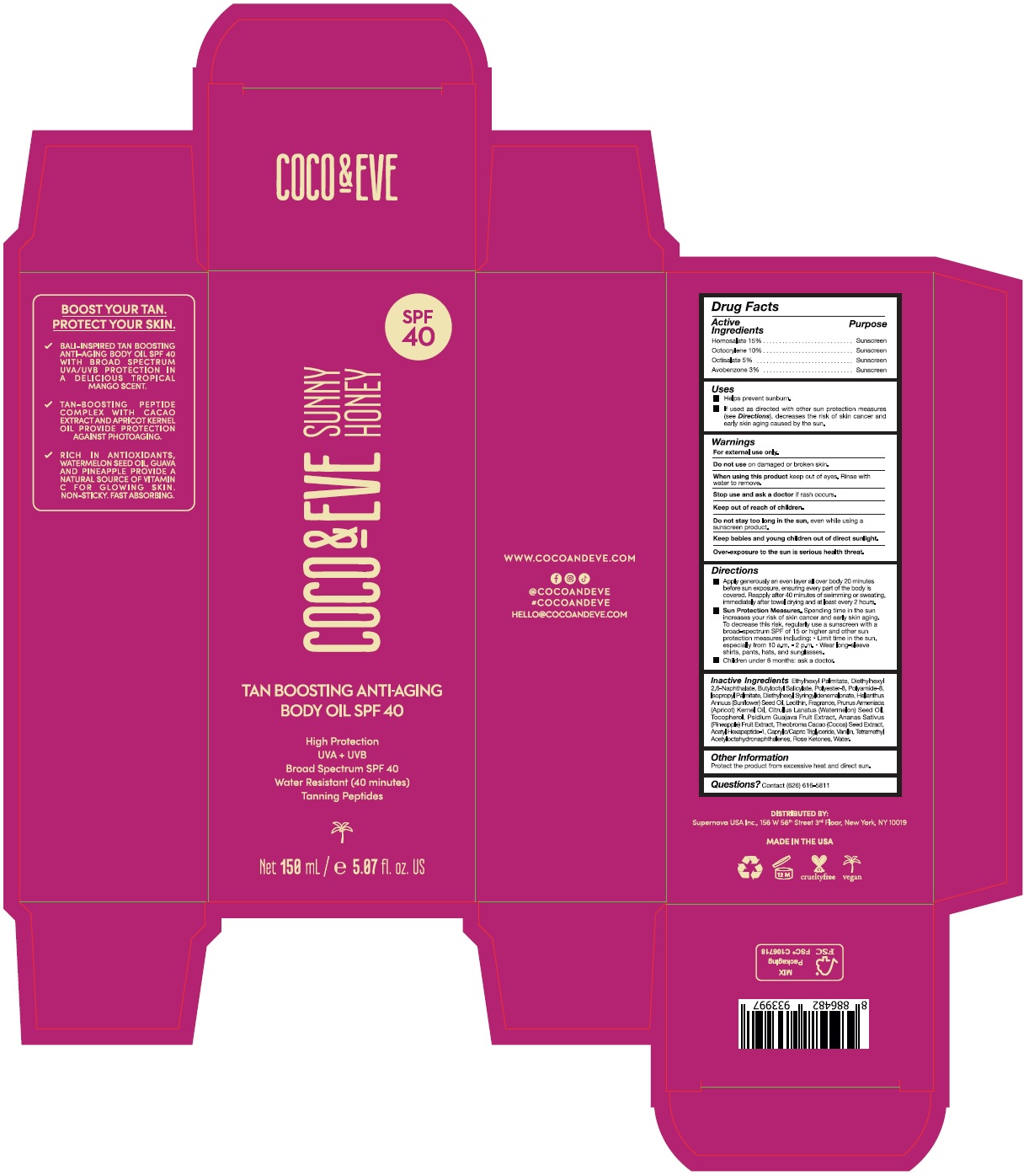 DRUG LABEL: coco and eve tan boosting anti-aging body oil spf 40
NDC: 82931-013 | Form: LOTION
Manufacturer: Supernova USA Inc.
Category: otc | Type: HUMAN OTC DRUG LABEL
Date: 20241204

ACTIVE INGREDIENTS: HOMOSALATE 15 g/100 mL; OCTOCRYLENE 10 g/100 mL; OCTISALATE 5 g/100 mL; AVOBENZONE 3 g/100 mL
INACTIVE INGREDIENTS: ETHYLHEXYL PALMITATE; DIETHYLHEXYL 2,6-NAPHTHALATE; BUTYLOCTYL SALICYLATE; POLYESTER-8 (1400 MW, CYANODIPHENYLPROPENOYL CAPPED); POLYAMIDE-8 (4500 MW); ISOPROPYL PALMITATE; DIETHYLHEXYL SYRINGYLIDENEMALONATE; SUNFLOWER OIL; SOYBEAN LECITHIN; ETHYL VANILLIN; OCTAHYDROCOUMARIN; PIPERONAL; ETHYL MALTOL; SANDALORE; HEXYL SALICYLATE; 6,6-DIMETHOXY-2,5,5-TRIMETHYL-2-HEXENE; ETHYL LINALOOL; ISOCYCLEMONE E; BUTYLATED HYDROXYTOLUENE; HEXAMETHYLINDANOPYRAN; METHYL 2-NONYNOATE; APRICOT KERNEL OIL; WATERMELON SEED OIL; TOCOPHEROL; GUAVA; PINEAPPLE; COCOA; ACETYL HEXAPEPTIDE-1; MEDIUM-CHAIN TRIGLYCERIDES; VANILLIN; TETRAMETHYL ACETYLOCTAHYDRONAPHTHALENES; .ALPHA.-DAMASCONE, (E)-; .DELTA.-DAMASCONE; .BETA.-DAMASCENONE; WATER

COCO & EVE TAN BOOSTING ANTI-AGING BODY OIL SPF 40

Drug Facts

Active Ingredients
Homosalate 15%
Octocrylene 10%
Octisalate 5%
Avobenzone 3%

Purpose
Sunscreen
Sunscreen
Sunscreen
Sunscreen

Uses

- Helps prevent sunburn.
- If used as directed with other sun protection measures (see Directions), decreases the risk of skin cancer and early skin aging caused by the sun.

Warnings

For external use only.

Do not use on damaged or broken skin.

When using this product keep out of eyes. Rinse with water to remove.

Stop use and ask a doctor if rash occurs.

Keep out of reach of children.

Do not stay too long in the sun, even while using a sunscreen product.

Keep babies and young children out of direct sunlight.

Over-exposure to the sun is serious health threat.

Directions

- Apply generously an even layer all over body 20 minutes before sun exposure, ensuring every part of the body is covered. Reapply after 40 minutes of swimming or sweating, immediately after towel drying and at least every 2 hours.
- Sun Protection Measures. Spending time in the sun increases your risk of skin cancer and early skin aging. To decrease this risk, regularly use a sunscreen with a broad-spectrum SPF of 15 or higher and other sun protection measures including:
  - Limit time in the sun, especially from 10 a.m. - 2 p.m.
  - Wear long-sleeve shirts, pants, hats, and sunglasses.
- Children under 6 months: ask a doctor.

INACTIVE INGREDIENT

Inactive Ingredients Ethylhexyl Palmitate, Diethylhexyl 2,6-Naphthalate, Butyloctyl Salicylate, Polyester-8, Polyamide-8, Isopropyl Palmitate, Diethylhexyl Syringylidenemalonate, Helianthus Annuus (Sunflower) Seed Oil, Lecithin, Fragrance, Prunus Armeniaca (Apricot) Kernel Oil, Citrullus Lanatus (Watermelon) Seed Oil, Tocopherol, Psidium Guajava Fruit Extract, Ananas Sativus (Pineapple) Fruit Extract, Theobroma Cacao (Cocoa) Seed Extract, Acetyl Hexapeptide-1, Caprylic/Capric Triglyceride, Vanillin, Tetramethyl Acetyloctahydronaphthalenes, Rose Ketones, Water.

Other Information

Protect the product from excessive heat and direct sun.

Questions? Contact (626) 616-5811

PRINCIPAL DISPLAY PANEL

COCO & EVE

TAN BOOSTING ANTI-AGING
BODY OIL SPF 40

High Protection

UVA + UVB

Broad Spectrum SPF 40

Water Resistant (40 minutes)

Net 150 mL / e 5.07 fl. oz. US

SPF
40

COCO & EVE

SUNNY
HONEY

TAN BOOSTING ANTI-AGING
BODY OIL SPF 40

High Protection

UVA + UVB

Broad Spectrum SPF 40

Water Resistant (40 minutes)

Tanning Peptides

Net 150 mL / e 5.07 fl. oz. US